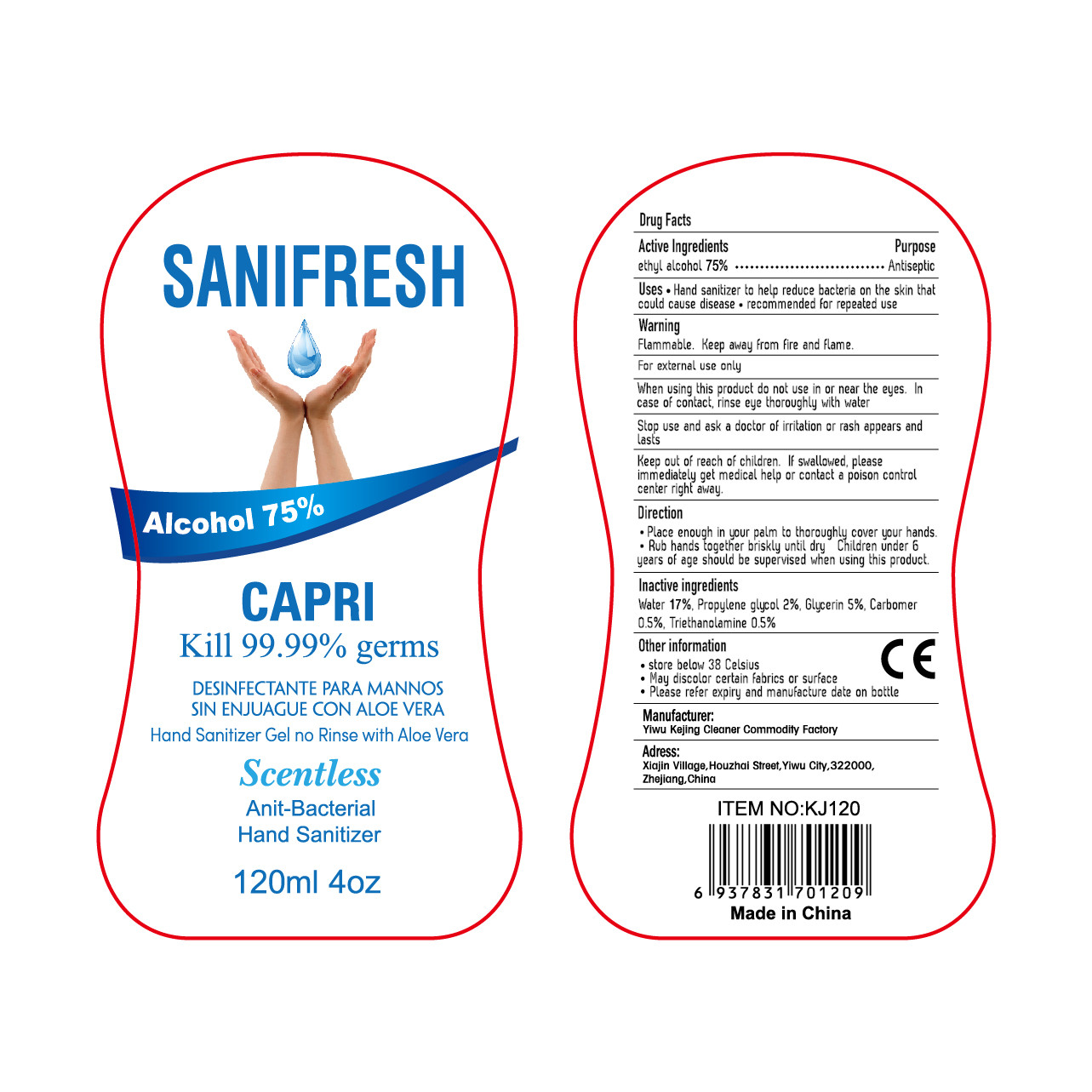 DRUG LABEL: Hand Sanitizer
NDC: 52687-002 | Form: GEL
Manufacturer: Yiwu Kejing Cleaning Products Factory
Category: otc | Type: HUMAN OTC DRUG LABEL
Date: 20200430

ACTIVE INGREDIENTS: ALCOHOL 90 mL/120 mL
INACTIVE INGREDIENTS: CARBOMER HOMOPOLYMER, UNSPECIFIED TYPE; GLYCERIN; TROLAMINE; WATER; PROPYLENE GLYCOL

DOSAGE AND ADMINISTRATION

store below 38 Celsius

keep out of reach of children section

PURPOSE

Disinfection
Sterilization
No Rinseing

ACTIVE INGREDIENT

70% Medical Alcohol

INACTIVE INGREDIENT

water17%, Propylene glycol 2%,glycerin5%, carbomer0.5%,triethanolamine0.5%

INDICATIONS AND USAGE

●Place enough in your palm to thoroughly cover your hands.
●Rub hands together briskly until dry Children under 6 years of age should be supervised when using this product.

WARNINGS

Flammable. Keep anway from fire and flame.
For external use only
When using this product do not use in or near the eyes. In case of contact, rinse eye thoroughly with walter
Stop use and ask a doctor of iritation or rash appears and Lasts
Keep out of reach of children. IF swallowed, please immediately get medical help or contact a poison controlcenter right away.